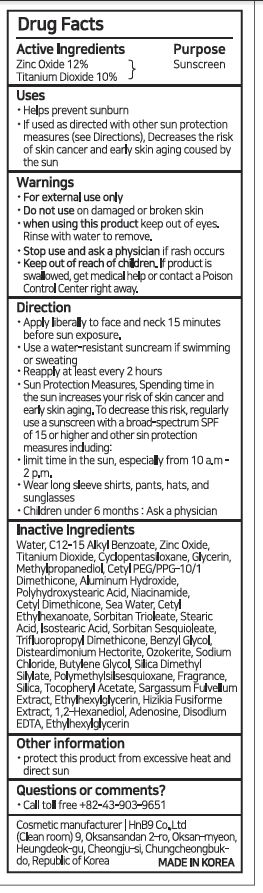 DRUG LABEL: ONALT PURE MILD SUNCREAM
NDC: 80564-0001 | Form: CREAM
Manufacturer: HnB9 Co., Ltd.
Category: otc | Type: HUMAN OTC DRUG LABEL
Date: 20200921

ACTIVE INGREDIENTS: TITANIUM DIOXIDE 10 g/100 mL; ZINC OXIDE 12 g/100 mL
INACTIVE INGREDIENTS: ALUMINUM HYDROXIDE; WATER; GLYCERIN

ACTIVE INGREDIENT

titanium dioxide, zinc oxide

PURPOSE

UV protection

skin whitening

wrinkle care

KEEP OUT OF REACH OF THE CHILDREN

WARNINGS

■ For external use only.

■ Do not use in eyes.

■ lf swallowed, get medical help promptly.

■ Stop use, ask doctor lf irritation occurs.

■ Keep out of reach of children.

DOSAGE AND ADMINISTRATION

for external use only

INACTIVE INGREDIENT

Water
C12-15 Alkyl Benzoate
Cyclopentasiloxane
Glycerin
Methylpropanediol
Cetyl PEG/PPG-10/1 Dimethicone
Aluminum Hydroxide
Polyhydroxystearic Acid
Niacinamide
Cetyl Dimethicone
Sea Water
Cetyl Ethylhexanoate
Sorbitan Trioleate
Stearic Acid
Isostearic Acid
Sorbitan Sesquioleate
Trifluoropropyl Dimethicone
Benzyl Glycol
Disteardimonium Hectorite
Ozokerite
Sodium Chloride
Butylene Glycol
Silica Dimethyl Silylate
Polymethylsilsesquioxane
Fragrance
Silica
Tocopheryl Acetate
Sargassum Fulvellum Extract
Ethylhexylglycerin
Hizikia Fusiforme Extract
1,2-Hexanediol
Adenosine
Disodium EDTA
Ethylhexylglycerin

INDICATIONS AND USAGE

apply proper amount to the skin